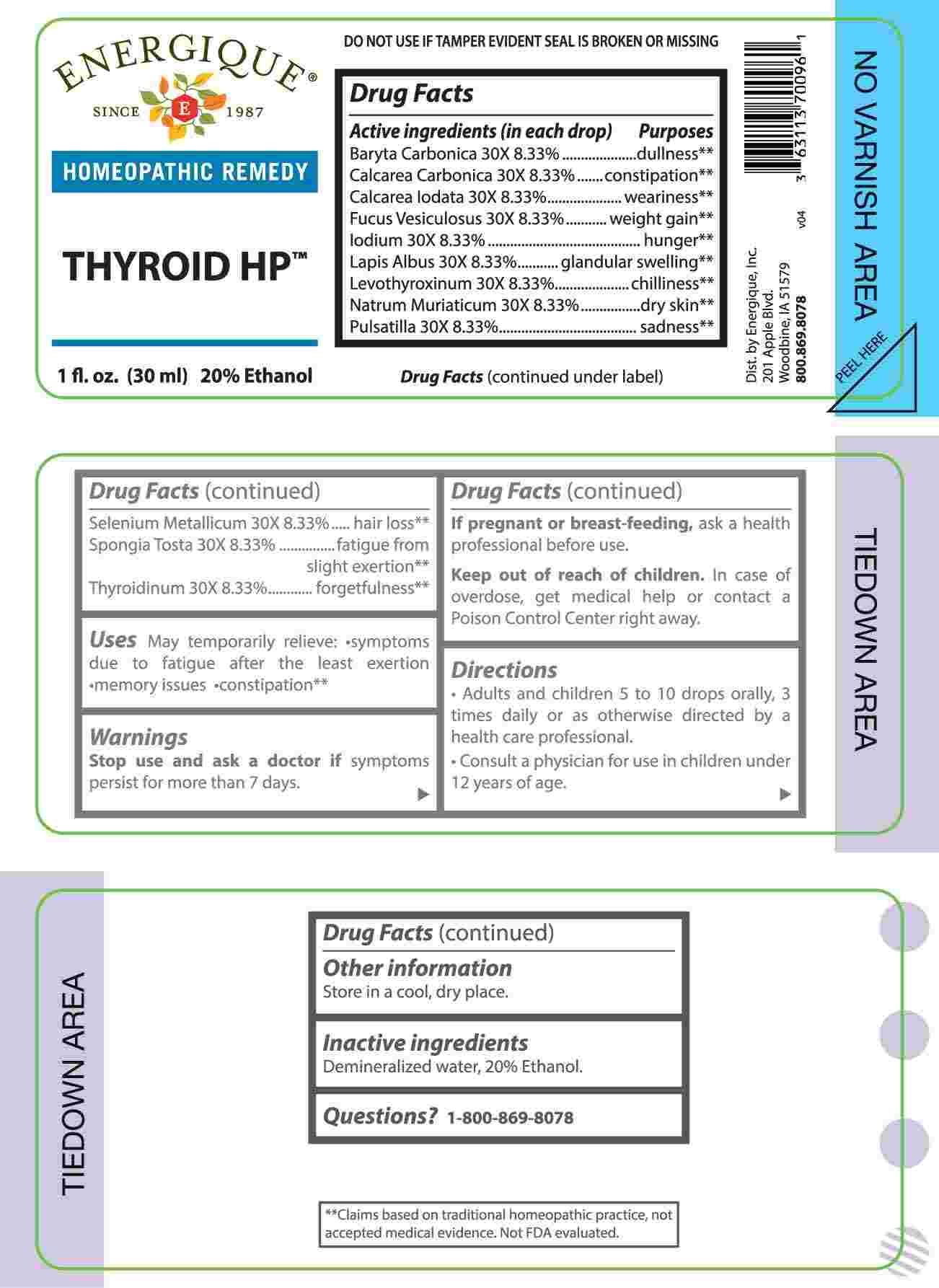 DRUG LABEL: Thyroid HP
NDC: 44911-0722 | Form: LIQUID
Manufacturer: Energique, Inc.
Category: homeopathic | Type: HUMAN OTC DRUG LABEL
Date: 20240930

ACTIVE INGREDIENTS: BARIUM CARBONATE 30 [hp_X]/1 mL; OYSTER SHELL CALCIUM CARBONATE, CRUDE 30 [hp_X]/1 mL; CALCIUM IODIDE 30 [hp_X]/1 mL; FUCUS VESICULOSUS 30 [hp_X]/1 mL; IODINE 30 [hp_X]/1 mL; CALCIUM HEXAFLUOROSILICATE 30 [hp_X]/1 mL; LEVOTHYROXINE 30 [hp_X]/1 mL; SODIUM CHLORIDE 30 [hp_X]/1 mL; PULSATILLA VULGARIS WHOLE 30 [hp_X]/1 mL; SELENIUM 30 [hp_X]/1 mL; SPONGIA OFFICINALIS SKELETON, ROASTED 30 [hp_X]/1 mL; THYROID 30 [hp_X]/1 mL
INACTIVE INGREDIENTS: WATER; ALCOHOL

DRUG FACTS:

ACTIVE INGREDIENTS:

(in each drop) Baryta Carbonica 30X 8.33%, Calcarea Carbonica 30X 8.33%, Calcarea Iodata 30X 8.33%, Fucus Vesiculosus 30X 8.33%, Iodium 30X 8.33%, Lapis Albus 30X 8.33%, Levothyroxinum 30X 8.33%, Natrum Muriaticum 30X 8.33%, Pulsatilla 30X 8.33%, Selenium Metallicum 30X 8.33%, Spongia Tosta 30X 8.33%, Thyroidinum 30X 8.33%.

PURPOSE:

Baryta Carbonica - dullness,** Calcarea Carbonica - constipation,** Calcarea Iodata - weariness,** Fucus Vesiculosus – weight gain,** Iodium - hunger,** Lapis Albus – glandular swelling,** Levothyroxinum - chilliness,** Natrum Muriaticum – dry skin,** Pulsatilla - sadness,** Selenium Metallicum – hair loss,** Spongia Tosta – fatigue from slight exertion,** Thyroidinum – forgetfulness**

**Claims based on traditional homeopathic practice, not accepted medical evidence. Not FDA evaluated.

USES:

May temporarily relieve: •symptoms due to fatigue after the least exertion •memory issues •constipation**

**Claims based on traditional homeopathic practice, not accepted medical evidence. Not FDA evaluated.

WARNINGS:

Stop use and ask a doctor if symptoms persist for more than 7 days.

If pregnant or breast-feeding, ask a health professional before use.

Keep out of reach of children. In case of overdose, get medical help or contact a Poison Control Center right away.

DO NOT USE IF TAMPER EVIDENT SEAL IS BROKEN OR MISSING

Store in a cool, dry place.

KEEP OUT OF REACH OF CHILDREN:

In case of overdose, get medical help or contact a Poison Control Center right away.

DIRECTIONS:

• Adults and children 5 to 10 drops orally, 3 times daily or as otherwise directed by a health care professional.

• Consult a physician for use in children under 12 years of age.

INACTIVE INGREDIENTS:

Demineralized water, 20% Ethanol.

QUESTIONS:

Dist. by Energique, Inc.

201 Apple Blvd

Woodbine, IA 51579

800.869.8078

PACKAGE LABEL DISPLAY:

ENERGIQUE

SINCE 1987

HOMEOPATHIC REMEDY

THYROID HP
1 fl. oz. (30 ml)